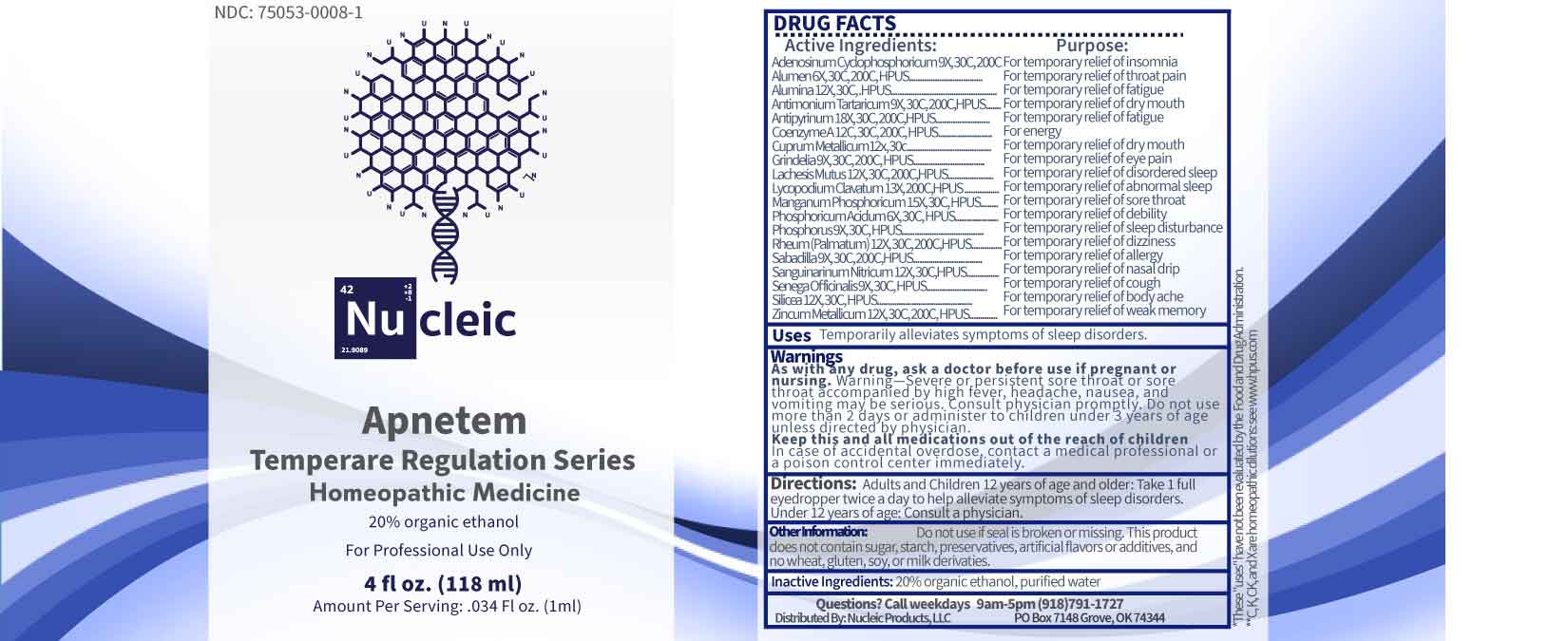 DRUG LABEL: Apnetem
NDC: 75053-0008 | Form: LIQUID
Manufacturer: Nucleic Products, LLC
Category: homeopathic | Type: HUMAN OTC DRUG LABEL
Date: 20250514

ACTIVE INGREDIENTS: PHOSPHORIC ACID 6 [hp_X]/1 mL; POTASSIUM ALUM 6 [hp_X]/1 mL; PHOSPHORUS 9 [hp_X]/1 mL; POLYGALA SENEGA ROOT 9 [hp_X]/1 mL; ADENOSINE CYCLIC PHOSPHATE 9 [hp_X]/1 mL; ANTIMONY POTASSIUM TARTRATE 9 [hp_X]/1 mL; GRINDELIA HIRSUTULA FLOWERING TOP 9 [hp_X]/1 mL; SCHOENOCAULON OFFICINALE SEED 9 [hp_X]/1 mL; ALUMINUM OXIDE 12 [hp_X]/1 mL; COPPER 12 [hp_X]/1 mL; SANGUINARINE NITRATE 12 [hp_X]/1 mL; SILICON DIOXIDE 12 [hp_X]/1 mL; LACHESIS MUTA VENOM 12 [hp_X]/1 mL; RHEUM PALMATUM ROOT 12 [hp_X]/1 mL; ZINC 12 [hp_X]/1 mL; LYCOPODIUM CLAVATUM SPORE 13 [hp_X]/1 mL; MANGANESE PHOSPHATE, DIBASIC 15 [hp_X]/1 mL; ANTIPYRINE 18 [hp_X]/1 mL; COENZYME A 12 [hp_C]/1 mL
INACTIVE INGREDIENTS: WATER; ALCOHOL

DRUG FACTS:

ACTIVE INGREDIENTS:

Adenosinum Cyclophosphoricum 9X, 30C, 200C HPUS, Alumen 6X, 30C, 200C HPUS, Alumina 12X, 30C HPUS, Antimonium Tartaricum 9X, 30C, 200C HPUS, Antipyrinum 18X, 30C, 200C HPUS, Coenzyme A 12C, 30C, 200C HPUS, Cuprum Metallicum 12X, 30C HPUS, Grindelia 9X, 30C, 200C HPUS, Lachesis Mutus 12X, 30C, 200C HPUS, Lycopodium Clavatum 13X, 200C HPUS, Manganum Phosphoricum 15X, 30C HPUS, Phosphoricum Acidum 6X, 30C HPUS, Phosphorus 9X, 30C HPUS, Rheum (Palmatum) 12X, 30C, 200C HPUS, Sabadilla 9X, 30C, 200C HPUS, Sanguinarinum Nitricum 12X, 30C HPUS, Senega Officinalis 9X, 30C HPUS, Silicea 12X, 30C HPUS, Zincum Metallicum 12X, 30C, 200C HPUS.

PURPOSE:

Adenosinum Cyclophosphoricum – For temporary relief of insomnia, Alumen – For temporary relief of throat pain, Alumina – For temporary relief of fatigue, Antimonium Tartaricum – For temporary relief of dry mouth, Antipyrinum – For temporary relief of fatigue, Coenzyme A – For energy, Cuprum Metallicum – For temporary relief of dry mouth, Grindelia – For temporary relief of eye pain, Lachesis Mutus – For temporary relief of disordered sleep, Lycopodium Clavatum – For temporary relief of abnormal sleep, Manganum Phosphoricum – For temporary relief of sore throat, Phosphoricum Acidum – For temporary relief of debility, Phosphorus – For temporary relief of sleep disturbance, Rheum (Palmatum) – For temporary relief of dizziness, Sabadilla – For temporary relief of allergy, Sanguinarinum Nitricum – For temporary relief of nasal drip, Senega Officinalis – For temporary relief of cough, Silicea – For temporary relief of body ache, Zincum Metallicum – For temporary relief of weak memory

USES:

Temporarily alleviates symptoms of sleep disorders.

These "uses" have not been evaluated by the Food and Drug Administration.

WARNINGS:

As with any drug, ask a doctor before use if pregnant or nursing. Warning - Severe or persistent sore throat or sore throat accompanied by high fever, headache, nausea, and vomiting may be serious. Consult physicians promptly. Do not use more than 2 days or administer to children under 3 years of age unless directed by physician.

Keep this and all medications out of the reach of children.

In case of accidental overdose, contact a medical professional or poison control center immediately.

OTHER INFORMATION:

Do not use if seal is broken or missing. This product does not contain sugar, starch, preservatives, artificial flavors or additives, and no wheat, gluten, soy, or milk derivatives.

KEEP OUT OF REACH OF CHILDREN:

In case of accidental overdose, contact a medical professional or poison control center immediately.

DIRECTIONS:

Adults and Children 12 years of age and older: Take one full eyedropper twice a day to help alleviate symptoms of sleep disorders. Under 12 years of age: Consult a physician.

INACTIVE INGREDIENTS:

20% organic ethanol, purified water

QUESTIONS:

Call weekdays 9am-5pm (918)791-1727

Distributed by:
Nucleic Products, LLC

PO Box 7148 Grove, OK 74344

PACKAGING LABEL DISPLAY:

NDC: 75053-0008-1

Nu cleic

Apnetem

Temperare Regulation Series

Homeopathic Medicine

For Professional Use Only

4 fl oz. (118 ml)